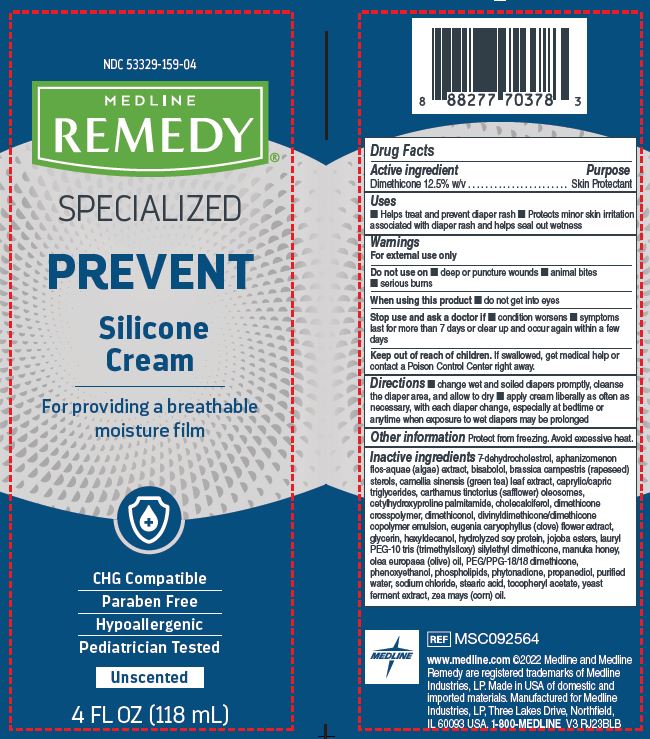 DRUG LABEL: Medline
NDC: 53329-159 | Form: CREAM
Manufacturer: Medline Industries, LP
Category: otc | Type: HUMAN OTC DRUG LABEL
Date: 20240501

ACTIVE INGREDIENTS: DIMETHICONE 125 mg/1 mL
INACTIVE INGREDIENTS: DIMETHICONOL (2000 CST); JOJOBA OIL, RANDOMIZED; PHENOXYETHANOL; MEDIUM-CHAIN TRIGLYCERIDES; CHOLECALCIFEROL; CLOVE; HEXYLDECANOL; HYDROLYZED SOY PROTEIN (ENZYMATIC; 2000 MW); APHANIZOMENON FLOSAQUAE; CARTHAMUS TINCTORIUS (SAFFLOWER) OLEOSOMES; GLYCERIN; OLIVE OIL; HONEY; CETYLHYDROXYPROLINE PALMITAMIDE; PEG/PPG-18/18 DIMETHICONE; PHYTONADIONE; PROPANEDIOL; STEARIC ACID; ALPHA-TOCOPHEROL ACETATE; YEAST, UNSPECIFIED; CORN OIL; WATER; SODIUM CHLORIDE; OMEGA-3 FATTY ACIDS; LEVOMENOL; RAPESEED STEROL; GREEN TEA LEAF; 7-DEHYDROCHOLESTEROL

159 Remedy Specialized Silicone Cream

Active ingredient

Dimethicone 12.5% w/v

Purpose

Skin protectant

Uses

- helps treat and prevent diaper rash
- protects minor skin irritation with diaper rash and helps seal out wetness

Warnings

For external use only

Do not use on

- deep or puncture wounds
- animal bites
- serious burns

When using this product

- do not get into eyes

Stop use and ask a doctor if

- condition worsens
- symptoms last for more than 7 days or clear up and occur again within a few days

Keep out of reach of children.

If swallowed, get medical help or contact a Poison Control Center right away.

Directions

- change wet and soiled diapers promptly, cleans the diaper area and allow to dry
- apply cream liberally as often as necessary with each diaper change esspecially at bedtime or anytime when exposure to wet diapers may be prolonged

Other information

- protect from freezing, avoid excessive heat

Inactive ingredients

7-dehydrocholestrol, aphanizomenon flos-aquae (algae) extract, bisabolol, brassica campestris (rapeseed) sterols, camellia sinensis (green tea) leaf extract, caprylic/capric triglycerides, carthamus tinctorius (safflower) oleosomes, cetylhydroxyproline palmitamide, cholecalciferol, dimethicone crosspolymer, dimethiconol, divinyldimethicone/dimethicone copolymer emulsion, eugenia caryophyllus (clove) flower extract, glycerin, hexyldecanol, hydrolyzed soy protein, jojoba esters, lauryl PEG-10 tris (trimethylsiloxy) silylethyl dimethicone, manuka honey, olea europaea (olive) oil, PEG/PPG-18/18 dimethicone, phenoxyethanol, phospholipids, phytonadione, propanediol, purified water, sodium chloride, stearic acid, tocopheryl acetate, yeast ferment extract, zea mays (corn) oil.

Manufacturing Information

Manufactured for:

Medline Industries, LP

Three Lakes Drive, Northfield, IL 60093 USA

Made in USA of domestic and imported materials

www.medline.com

1-800-MEDLINE (633-5463)

REF: MSC092564

V3 RJ23BLB